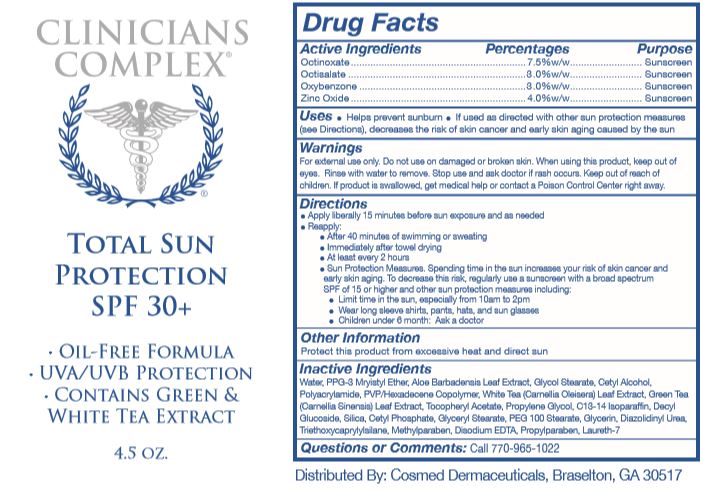 DRUG LABEL: Total Sun Protection
NDC: 61352-004 | Form: LOTION
Manufacturer: Cosmed Dermaceuticals, Inc.
Category: otc | Type: HUMAN OTC DRUG LABEL
Date: 20251111

ACTIVE INGREDIENTS: OCTINOXATE 75 mg/1 g; OCTISALATE 30 mg/1 g; OXYBENZONE 30 mg/1 g; ZINC OXIDE 40 mg/1 g
INACTIVE INGREDIENTS: WATER; ALOE VERA LEAF; PPG-3 MYRISTYL ETHER; GLYCOL STEARATE; CETYL ALCOHOL; POLYACRYLAMIDE (10000 MW); HEXADECYL POVIDONE (4 HEXADECYL BRANCHES/REPEAT); CAMELLIA OLEIFERA LEAF; CAMELLIA SINENSIS WHOLE; .ALPHA.-TOCOPHEROL ACETATE; PROPYLENE GLYCOL; C13-14 ISOPARAFFIN; DECYL GLUCOSIDE; SILICON DIOXIDE; CETYL PHOSPHATE; GLYCERYL MONOSTEARATE; PEG-100 STEARATE; GLYCERIN; DIAZOLIDINYL UREA; TRIETHOXYCAPRYLYLSILANE; METHYLPARABEN; EDETATE DISODIUM; PROPYLPARABEN; LAURETH-7

Clinicians Complex Total Sun Protection SPF 30+

Active Ingredients

Octinoxate 7.5% w/w

Octisalate 3.0% w/w

Oxybenzone 3.0% w/w

Zinc Oxide 4.0% w/w

Purpose

Sunscreen

Uses

• Helps prevent sunburn

• If used as directed with other sun protection measures (see Directions), decreases the risk of skin cancer and early skin aging caused by the sun

Warnings

For external use only. Do not use on damaged or broken skin. When using this product keep out of eyes. Rinse with water to remove. Stop use and ask doctor if rash occurs. Keep out of reach of children. If product is swalled, get medical help or contact a Poison Control Center right away.

Keep out of reach of children.

Directions

• Apply liberally 15 minutes before sun exposure and as needed

• Reapply:

• After 40 minutes of swimming or sweating

• Immediately after towel drying

• At least every 2 hours

• Sun Protection Measures. Spending time in the sun increases your risk of skin cancer and early aging. To decrease this risk, regularly use

a sunscreen with a broad spectrum SPF of 15 or higher and other sun protection measures including:

• Limit time in the sun, especially from 10am to 2pm

• Wear long sleeve shirts, pants, hats, and sun glasses

• Children under 6 months: Ask a doctor

Other Information

Protect this product from excessive heat and direct sun

Questions or Comments:

Call 770-965-1022

Inactive Ingredients

Water, PPG-3 Myristyl Ether, Aloe Barbadensis Leaf Extract, Glycol Stearate, Cetyl Alcohol, Polyacrylamide, PVP/Hexadecene Copolymer, White Tea (Camellia Oleisera) Leaf Extract, Green Tea (Camellia Sinensis) Leaf Extract, Tocopheryl Acetate, Propylene Glycol, C13-14 Isoparaffin, Decyl Glucoside, Silica, Cetyl Phosphate, Glyceryl Stearate, PEG 100 Stearate, Glycerin, Diazolidinyl Urea, Triethoxycaprylylsilane, Methylparaben, Disodium EDTA, Propylparaben, Laureth-7